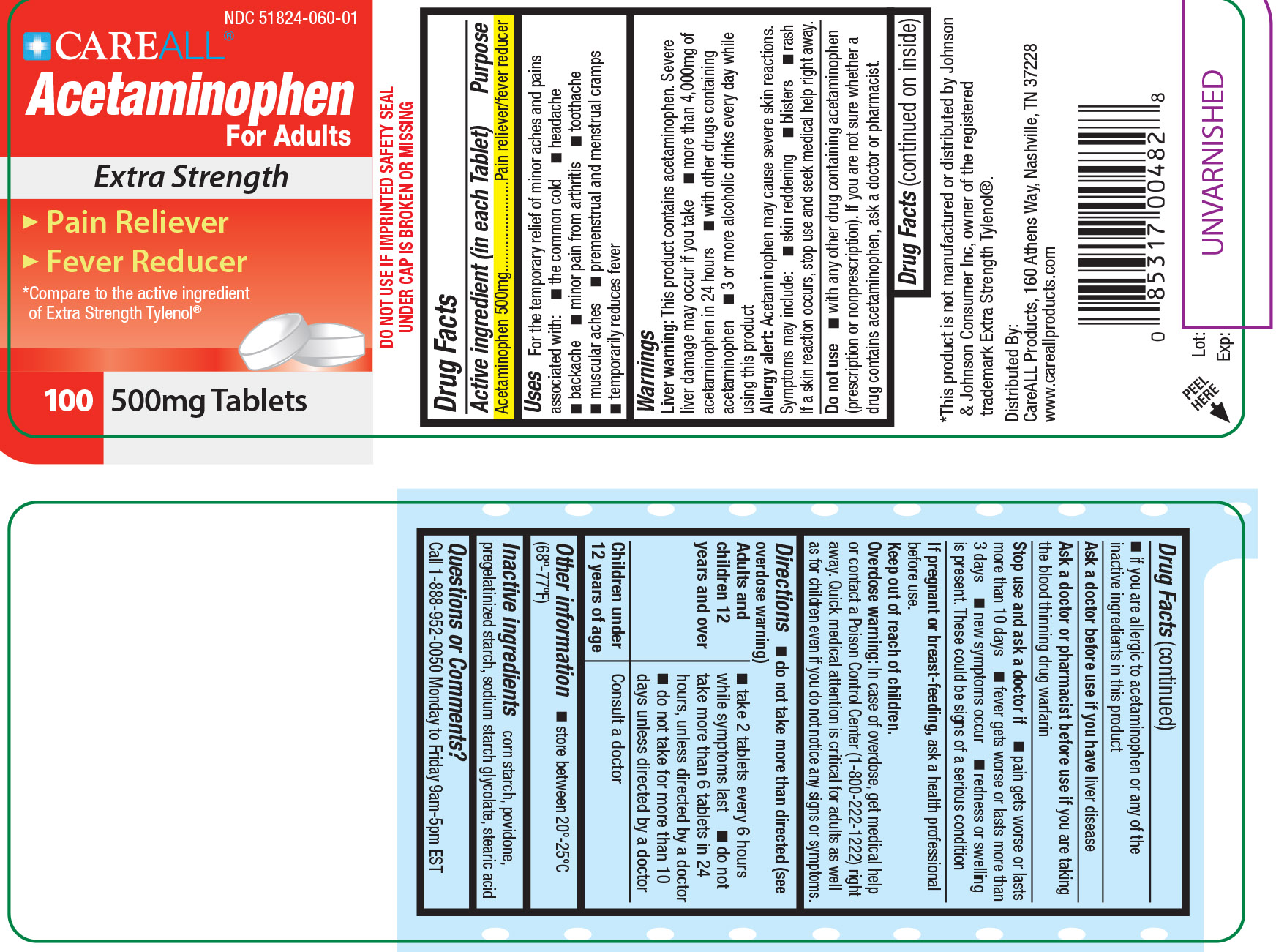 DRUG LABEL: CareALL Acetaminophen

NDC: 51824-060 | Form: TABLET
Manufacturer: New World Imports, Inc
Category: otc | Type: HUMAN OTC DRUG LABEL
Date: 20251222

ACTIVE INGREDIENTS: ACETAMINOPHEN 500 mg/1 1
INACTIVE INGREDIENTS: STARCH, CORN; STEARIC ACID; POVIDONE; SODIUM STARCH GLYCOLATE TYPE A POTATO

Drug Facts

Active Ingredient

Acteminophen 500 mg

Purpose

Pain reliever / Fever reducer

Keep out of reach of Children

Overdose warning: In case of overdose, get medical help or contact a Poison Control Center (1-800-222-1222) right away. Quick medical attention is critical for adults as well as for children even if you don't notice any signs or symptoms.

Uses

For the temporary of minor aches and pains associated with: common cold, headache, toothache, muscular aches, backache, arthritis, premenstrual and menstrual cramps

Temporarily reduces fever.

Warnings

Liver Warning:This product contains acetaminophen. Severe liver damage may occur if you take:

-Adults take more than 4,000mg of Acetaminophen in 24 hours

-with other drugs containing acetaminophen

-3 or more alcoholic drinks every day while using this product

Allergy Alert:Acetaminophen may cause severe skin reactions. Symptoms may include: skin reddening, blisters, rash. If a skin reaction occurs, stop use and seek medical help right away.

Do not use:

-If you are allergic to Acetaminophen

-With other products containing acetaminophen (prescription or nonprescription). If you are not sure whether a drug contains acetaminophen, ask a doctor or pharmacist.

Ask a doctor before use if you haveliver disease

Ask a doctor or pharmacist before use if youare taking the blood thinning drug warfarin

Stop use and ask a doctor if:

-Symptoms do not improve

-Pain gets worse or lasts for more than 10 days

-Fever gets worse or lasts for more than 3 days

-New symptoms occur

-Redness or swelling is present

-A rare sensitivity reaction occurs

If pregnant of breast-feeding,ask a health professional before use.

Do not use more than directed (see overdose warning)

Adults and children 12 years of age and older: Take 2 tablets every 6 hours as needed. Do not take more than 6 tablets in 24 hours, unless directed by a doctor.

Do not take for more than 10 days unless directed by a doctor.

Children under 12 years of age: consult a doctor

INACTIVE INGREDIENT

corn starch, povidone, pregelatinized starch, sodium starch glycolate, stearic acid